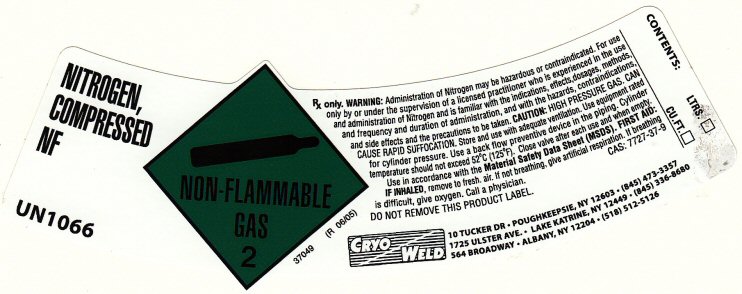 DRUG LABEL: NITROGEN
NDC: 76366-002 | Form: GAS
Manufacturer: Cryo Weld Corporation
Category: prescription | Type: HUMAN PRESCRIPTION DRUG LABEL
Date: 20120521

ACTIVE INGREDIENTS: NITROGEN 99 L/100 L

Nitrogen Label

NITROGEN NF COMPRESSED UN 1066 NON-FLAMMABLE-2 37049 R 06/05)
Rx ONLY. WARNING: ADMINISTRATION OF NITROGEN MAY BE HAZARDOUS OR CONTRAINDICATED. FOR USE ONLY BY OR UNDER THE SUPERVISION OF A LICENSED PRACTITIONER WHO IS EXPERIENCED IN THE USE AND ADMINISTRATION OF NITROGEN AND IS FAMILIAR WITH THE INDICATIONS, EFFECTS, DOSAGES, METHODS, AND FREQUENCY AND DURATION OF ADMINISTRATION, AND WITH THE SIDE EFFECTS AND THE PRECAUTIONS TO BE TAKEN.
CAUTION; HIGH PRESSURE GAS. CAN CAUSE RAPID SUFFOCATION. STORE AND USE WITH ADEQUATE VENTILATION. USE EQUIPMENT RATED FOR CYLINDER PRESSURE. USE A BACK FLOW PREVENTIVE DEVICE IN THE PIPING. CYLINDER TEMPERATURE SHOULD NOT EXCEED 52 DEGREES C (125 DEGREES F) CLOSE VALVE AFTER EACH USE AND WHEN EMPTY. USE IN ACCORDANCE WITH THE MATERIAL SAFETY DATA SHEET (MSDS) FIRST AID: IF INHALED, REMOVE TO FRESH. AIR. IF NOT BREATHING, GIVE ARTIFICIAL RESPIRATION. IF BREATHING IS DIFFICULT, GIVE OXYGEN. CALL A PHYSICIAN.

CAS: 7727-37-9 DO NOT REMOVE THIS PRODUCT LABEL.

CRYO WELD 10 TUCKER DR, POUGHKEEPSIE, NY 12603, (845) 473-3357

1725 ULSTER AVE, LAKE KATRINE, NY 12449, (845) 336-336-8680

564 BROADWAY, ALBANY, NY 12204, (518) 512-5126

CONTENTS: LTRS._________ CU. FT. _________